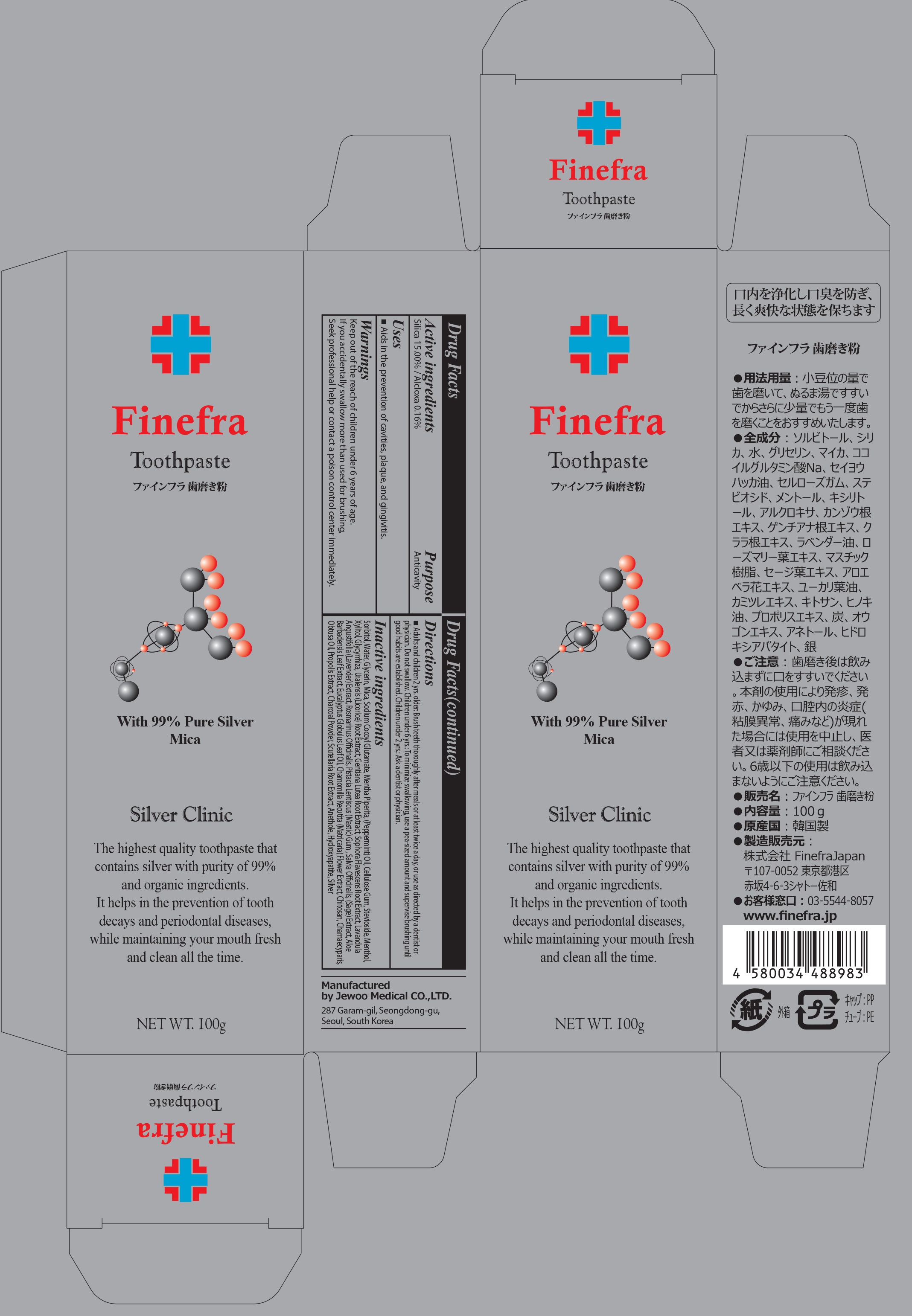 DRUG LABEL: Finefra Tooth
NDC: 69653-050 | Form: PASTE, DENTIFRICE
Manufacturer: Jewoo Medical Co,.Ltd
Category: otc | Type: HUMAN OTC DRUG LABEL
Date: 20181129

ACTIVE INGREDIENTS: SILICON DIOXIDE 15.0 g/100 g; ALCLOXA 0.16 g/100 g
INACTIVE INGREDIENTS: SORBITOL; Water

ACTIVE INGREDIENT

Active ingredients: Silica 15.00%, Alcloxa 0.16%

INACTIVE INGREDIENT

Inactive ingredients:

Sorbitol, Water, Glycerin, Mica, Sodium Cocoyl Glutamate, Mentha Piperita, (Peppermint) Oil, Cellulose Gum, Stevioside, Menthol, Xylitol, Glycyrrhiza, Uralensis (Licorice) Root Extract, Gentiana Lutea Root Extract, Sophora Flavescens Root Extract, Lavandula Angustifolia (Lavender) Extract, Rosmarinus Officinalis, Pistacia Lentiscus (Mastic) Gum , Salvia Officinalis, (Sage) Extract, Aloe Barbadensis Leaf Extract, Eucalyptus Globulus Leaf Oil, Chamomilla Recutita (Matricaria) Flower Extract, Chitosan, Chamaecyparis, Obtusa Oil, Propolis Extract, Charcoal Powder, Scutellaria Root Extract, Anethole, Hydroxyapatite, Silver

PURPOSE

Purpose: Anticavity

WARNINGS

Keep out of the reach of children under 6 years of age.

If you accidentally swallow more than used for brushing, Seek professional help or contact a poison control center immediately.

KEEP OUT OF REACH OF CHILDREN

Keep out of the reach of children under 6 years of age.

Uses

Aids in the prevention of cavities, plaque, and gingivitis.

Directions

Adults and children 2 yrs. older: Brush teeth thoroughly after meals or at least twice a day, or use as directed by a dentist or physician. Do not swallow. Children under 6 yrs.: To minimize swallowing, use a pea-sized amount and supervise brushing until good habits are established. Children under 2 yrs.: Ask a dentist or physician.